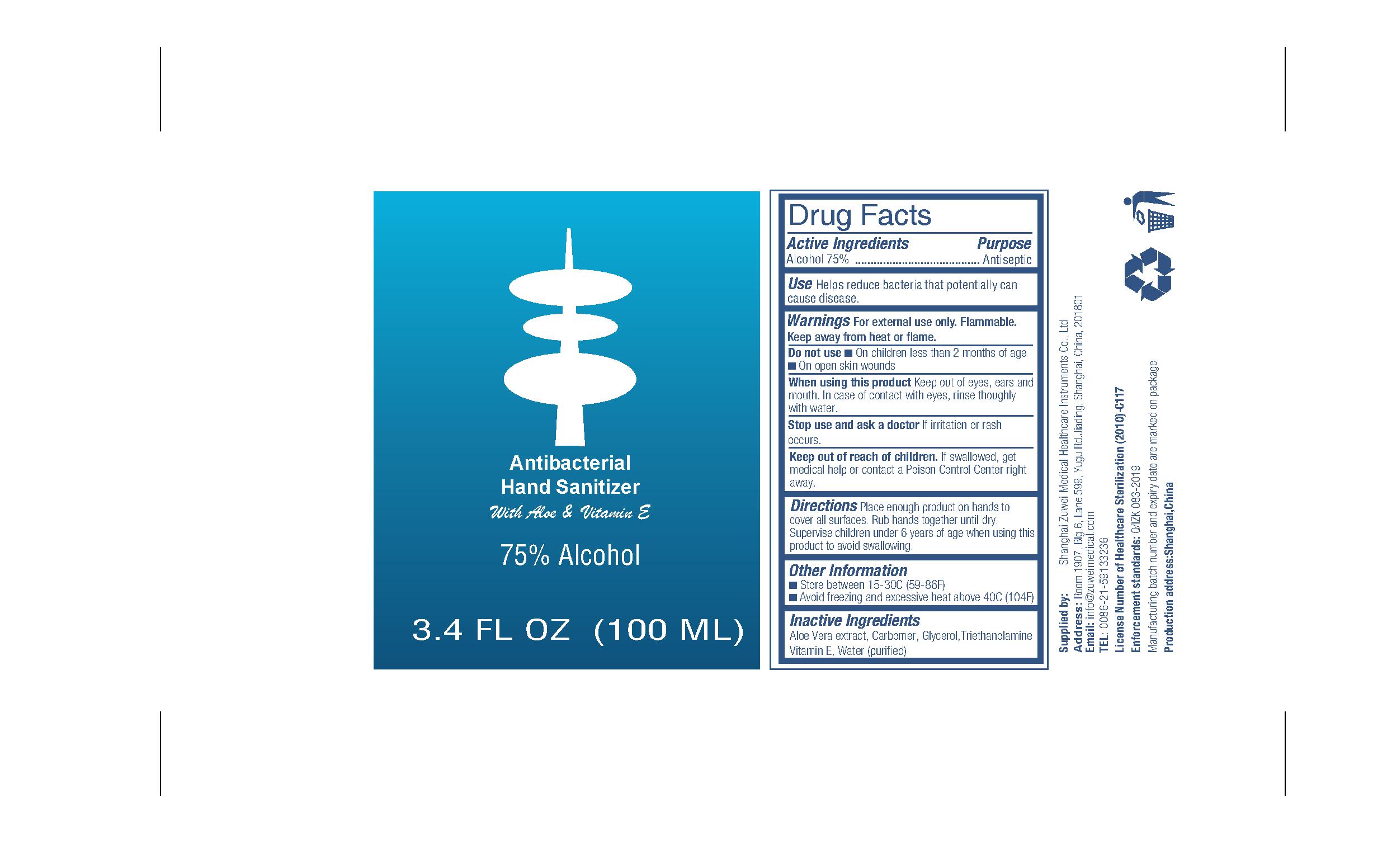 DRUG LABEL: Hand Sanitizer
NDC: 77204-001 | Form: GEL
Manufacturer: Shanghai Zuwei Medical Healthcare Instruments Co.,Ltd.
Category: otc | Type: HUMAN OTC DRUG LABEL
Date: 20200706

ACTIVE INGREDIENTS: ALCOHOL 75 mL/100 mL
INACTIVE INGREDIENTS: GLYCERIN 0.15 mL/100 mL; TRIETHANOLAMINE DODECYLBENZENESULFONATE 0.35 mL/100 mL; WATER 24 mL/100 mL; TOCOPHEROL 0.1 mL/100 mL; CARBOMER HOMOPOLYMER, UNSPECIFIED TYPE 0.3 mL/100 mL; ALOE VERA LEAF 0.1 mL/100 mL

Antibacterial Hand Sanitizer With Aloe & Vitamin E

Active Ingredients

Alcohol 75%

Purpose

Antiseptic

Use

Use Helps reduce bacteria that potentially can cause disease.

Warnings

For external use only. Flammable.
Keep away from heat or flame.

Do not use

- On children less than 2 months of age
- on open skin wounds

When using this product keep out of eyes, ears, and mouth. In case of contact with eyes, rinse eyes thoroughly with water.

Stop use and ask a doctor if irritation or rash occurs.

Keep out of reach of children. If swallowed, get medical help or contact a Poison Control Center right away.

Directions

Directions Place enough product on hands to cover all surfaces. Rub hands together until dry.

Supervise children under 6 years of age when using this product to avoid swallowing.

Other information

- Store between 15-30C (59-86F)
- Avoid freezing and excessive heat above 40C (104F)

Inactive ingredients

Inactive ingredients Aloe Vera extract, Carbomer, Glycerol, Triethanolamine, Vitamin E, Water(Purified)

Package Label - Principal Display Panel

100 ml NDC: 77204-001-01